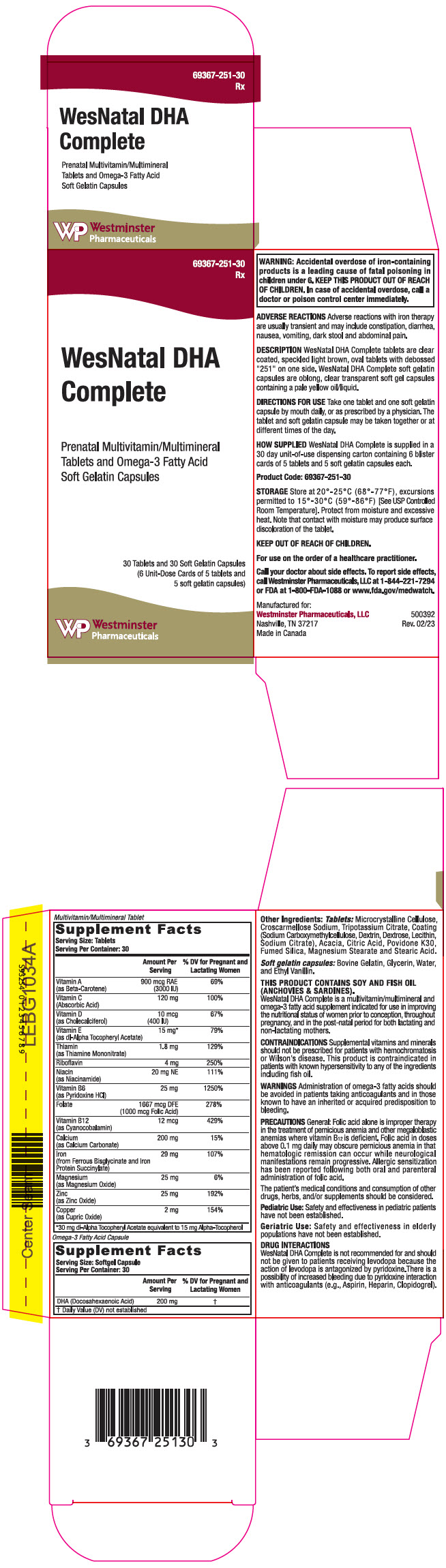 DRUG LABEL: WesNatal DHA Complete
NDC: 69367-251 | Form: KIT | Route: ORAL
Manufacturer: Westminster Pharmaceuticals, LLC
Category: other | Type: DIETARY SUPPLEMENT
Date: 20230413

ACTIVE INGREDIENTS: BETA CAROTENE 3000 [iU]/1 1; ASCORBIC ACID 120 mg/1 1; CHOLECALCIFEROL 400 [iU]/1 1; .ALPHA.-TOCOPHEROL ACETATE, DL- 30 mg/1 1; THIAMINE MONONITRATE 1.8 mg/1 1; RIBOFLAVIN 4 mg/1 1; NIACINAMIDE 20 mg/1 1; PYRIDOXINE HYDROCHLORIDE 25 mg/1 1; FOLIC ACID 1 mg/1 1; CYANOCOBALAMIN 12 ug/1 1; CALCIUM CARBONATE 200 mg/1 1; FERROUS BISGLYCINATE 29 mg/1 1; MAGNESIUM OXIDE 25 mg/1 1; ZINC OXIDE 25 mg/1 1; CUPRIC OXIDE 2 mg/1 1; DOCONEXENT 200 mg/1 1
INACTIVE INGREDIENTS: MICROCRYSTALLINE CELLULOSE; CROSCARMELLOSE SODIUM; POTASSIUM CITRATE TRIHYDRATE; CARBOXYMETHYLCELLULOSE SODIUM, UNSPECIFIED; ICODEXTRIN; DEXTROSE MONOHYDRATE; LECITHIN, SOYBEAN; SODIUM CITRATE, UNSPECIFIED FORM; ACACIA; CITRIC ACID MONOHYDRATE; POVIDONE K30; SILICON DIOXIDE; MAGNESIUM STEARATE; STEARIC ACID; GELATIN TYPE B BOVINE (200 BLOOM); GLYCERIN; WATER; ETHYL VANILLIN

WesNatal DHA Complete

STATEMENT OF IDENTITY

Multivitamin/Multimineral Tablet

Supplement Facts
Serving Size: Tablets
Serving Per Container: 30
 | Amount Per Serving | % DV for Pregnant and Lactating Women
Vitamin A (as Beta-Carotene) | 900 mcg RAE (3000 IU) | 69%
Vitamin C (Abscorbic Acid) | 120 mg | 100%
Vitamin D (as Cholecalciferol) | 10 mcg (400 IU) | 67%
Vitamin E (as dl-Alpha Tocopheryl Acetate) | 15 mg [30 mg dl-Alpha Tocopheryl Acetate equivalent to 15 mg Alpha-Tocopherol] | 79%
Thiamin (as Thiamine Mononitrate) | 1.8 mg | 129%
Riboflavin | 4 mg | 250%
Niacin (as Niacinamide) | 20 mg NE | 111%
Vitamin B6 (as Pyridoxine HCl) | 25 mg | 1250%
Folate | 1667 mcg DFE (1000 mcg Folic Acid) | 278%
Vitamin B12 (as Cyanocobalamin) | 12 mcg | 429%
Calcium (as Calcium Carbonate) | 200 mg | 15%
Iron (from Ferrous Bisglycinate and Iron Protein Succinylate) | 29 mg | 107%
Magnesium (as Magnesium Oxide) | 25 mg | 6%
Zinc (as Zinc Oxide) | 25 mg | 192%
Copper (as Cupric Oxide) | 2 mg | 154%

Omega-3 Fatty Acid Capsule

Supplement Facts
Serving Size: Softgel Capsule
Serving Per Container: 30
 | Amount Per Serving | % DV for Pregnant and Lactating Women
DHA (Docosahexaenoic Acid) | 200 mg | [Daily Value (DV) not established]

Other Ingredients: Tablets: Microcrystalline Cellulose, Croscarmellose Sodium, Tripotassium Citrate, Coating (Sodium Carboxymethylcellulose, Dextrin, Dextrose, Lecithin, Sodium Citrate), Acacia, Citric Acid, Povidone K30, Fumed Silica, Magnesium Stearate and Stearic Acid.

Soft gelatin capsules: Bovine Gelatin, Glycerin, Water, and Ethyl Vanillin.

THIS PRODUCT CONTAINS SOY AND FISH OIL (ANCHOVIES & SARDINES).

WesNatal DHA Complete is a multivitamin/multimineral and omega-3 fatty acid supplement indicated for use in improving the nutritional status of women prior to conception, throughout pregnancy, and in the post-natal period for both lactating and non-lactating mothers.

CONTRAINDICATIONS

Supplemental vitamins and minerals should not be prescribed for patients with hemochromatosis or Wilson's disease. This product is contraindicated in patients with known hypersensitivity to any of the ingredients including fish oil.

WARNINGS

Administration of ometa-3 fatty acids should be avoided in patients taking anticoagulants and in those known to have an inherited or acquired predisposition to bleeding.

PRECAUTIONS

General

Folic acid alone is improper therapy in the treatment of pernicious anemia and other megaloblastic anemias where vitamin B12 is deficient. Folic acid in doses above 0.1 mg daily may obscure pernicious anemia in that hematologic remission can occur while neurological manifestations remain progressive. Allergic sensitization has been reported following both oral and parenteral administration of folic acid.

The patient's medical conditions and consumption of other drugs, herbs, and/or supplements should be considered.

Pediatric Use

Safety and effectiveness in pediatric patients have not been established.

Geriatric Use

Safety and effectiveness in elderly populations have not been established.

DRUG INTERACTIONS

WesNatal DHA Complete is not recommended for and should not be given to patients receiving levodopa because the action of levodopa is antagonized by pyridoxine. There is a possibility of increased bleeding due to pyridoxine interaction with anticoagulants (e.g., Aspirin, Heparin, Clopidogrel).

WARNINGS

WARNING: Accidental overdose of iron-containing products is a leading cause of fatal poisoning in children under 6. KEEP THIS PRODUCT OUT OF REACH OF CHILDREN. In case of accidental overdose, call a doctor or poison control center immediately.

ADVERSE REACTIONS

Adverse reactions with iron therapy are usually transient and may include constipation, diarrhea, nausea, vomiting, dark stool and abdominal pain.

DESCRIPTION

WesNatal Complete tablets are clear coated, speckled light brown, oval tablets with debossed "251" on one side. WesNatal DHA Complete soft gelatin capsules are oblong, clear transparent soft gel capsules containing a pale yellow oil/liquid.

DIRECTIONS FOR USE

Take one tablet and one soft gelatin capsule by mouth daily, or as prescribed by a physician. The tablet and soft gelatin capsule may be taken together or at different times of the day.

HOW SUPPLIED

WesNatal DHA Complete is supplied in a 30 day unit-of-use dispensing carton containing 6 blister cards of 5 tablets and 5 soft gelatin capsules each.

Product Code: 69367-251-30

STORAGE

Store at 20°-25°C (68°-77°F), excursions permitted to 15°-30°C (59°-86°F) [See USP Controlled Room Temperature]. Protect from moisture and excessive heat. Note that contact with moisture may produce surface discoloration of the tablet.

KEEP OUT OF REACH OF CHILDREN.

For use on the order of a healthcare practitioner.

Call your doctor about side effects. To report side effects, call Westminster Pharmaceuticals, LLC at 1-844-221-7294 or FDA at 1-800-FDA-1088 or www.fda.gov/medwatch.

Manufactured for:
Westminster Pharmaceuticals, LLC
Nashville, TN 37217
Made in Canada

500392
Rev. 02/23

PRINCIPAL DISPLAY PANEL - Kit Carton

69367-251-30
Rx

WesNatal DHA
Complete

Prenatal Multivitamin/Multimineral
Tablets and Omega-3 Fatty Acid
Soft Gelatin Capsules

30 Tablets and 30 Soft Gelatin Capsules
(6 Unit-Dose Cards of 5 tablets and
5 soft gelatin capsules)

Westminster
Pharmaceuticals